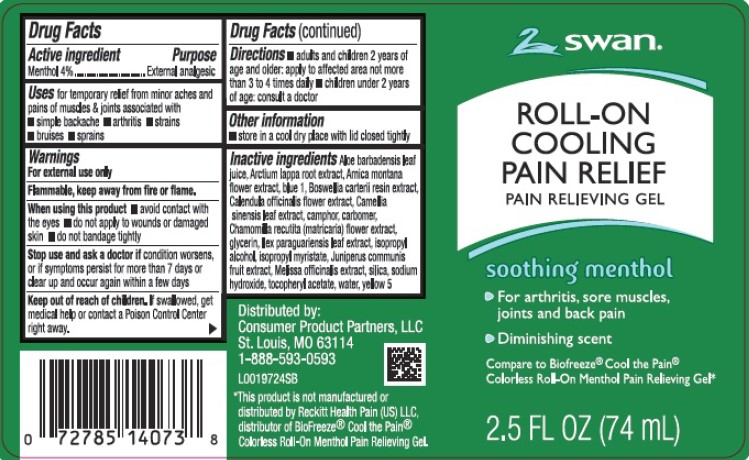 DRUG LABEL: Gel Cooling Pain Relief
NDC: 11344-894 | Form: GEL
Manufacturer: Consumer Product Partners, LLC
Category: otc | Type: HUMAN OTC DRUG LABEL
Date: 20250403

ACTIVE INGREDIENTS: MENTHOL 40 mg/1 mL
INACTIVE INGREDIENTS: ALOE VERA LEAF; ARCTIUM LAPPA ROOT; ARNICA MONTANA FLOWER; FD&C BLUE NO. 1; FRANKINCENSE; CALENDULA OFFICINALIS FLOWER; GREEN TEA LEAF; CAMPHOR (NATURAL); CARBOMER HOMOPOLYMER, UNSPECIFIED TYPE; CHAMOMILE; GLYCERIN; ILEX PARAGUARIENSIS LEAF; ISOPROPYL ALCOHOL; ISOPROPYL MYRISTATE; JUNIPER BERRY; MELISSA OFFICINALIS WHOLE; SILICON DIOXIDE; SODIUM HYDROXIDE; .ALPHA.-TOCOPHEROL ACETATE; WATER; FD&C YELLOW NO. 5

Swan 894.001/894AA rev 1
Cooling Pain Relief Gel

Active ingredient

Menthol 4%

Purpose

External analgesic

Uses

for temporary relief from minor aches and pains of muscles & joints associated with

- simple backache
- arthritis
- strains
- bruises
- sprains

Warnings

For external use only

Flammable, keep away from fire or flame.

When using this product

- avoid contact with the eyes
- do not apply to wounds or damaged skin
- do not bandage tightly

Stop use and ask a doctor if

condition worsens, or if symptoms persist for more than 7 days or clear up and occur again within a few days

Keep out of reach of children.

If swallowed, get medical help or contact a Poison Control Center right away.

Directions

- adults and children 2 years of age and older: apply to affected area not more than 3 to 4 times daily
- children under 2 years of age: consult a doctor

Other information

store in a cool dry place with lid closed tightly

Inactive ingredients

Aloe barbadensis leaf juice, Arctium lappa root extract, Arnica montana flower extract, blue 1, Boswellia carterii resin extract, Calendula officinalis flower extract, Camellia sinensis leaf extract, camphor, carbomer, Chamomilla recutita (matricaria) flower extract, glycerin, llex paraguariensis leaf extract, isopropyl alcohol, isopropyl myristate, Juniperus communis fruit extract, Melissa officinalis extract, silica, sodium hydroxide, tocopheryl acetate, water, yellow 5

Adverse reaction

Distributed by: Consumer Product Partners, LLC

St. Louis, MO 63114

1-888-593-0593

Disclaimer

*This product is not manufactured or distributed by Reckitt Health Pain (US) LLC, distributor of BioFreeze®Cool the Pain®Colorless Roll-On Menthol Pain Relieving Gel.

Principal display panel

swan®

ROLL-ON COOLING PAIN RELIEF

PAIN RELIEVING GEL

soothing menthol

- For arthritis, sore muscles, joints and back pain
- Diminishing scent

Compare to Biofreeze®Cool the Pain®Colorless Roll-On Menthol Pain Relieveing Gel*

2.5 FL OZ (74 mL)